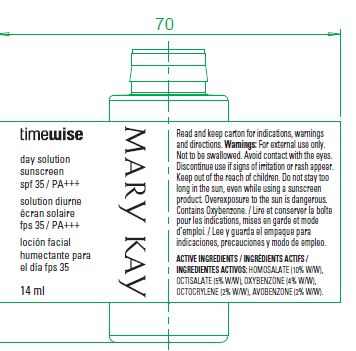 DRUG LABEL: Timewise Day Solution sunscreen SPF 35 14ml
NDC: 51531-8365 | Form: CREAM
Manufacturer: Mary Kay Inc.
Category: otc | Type: HUMAN OTC DRUG LABEL
Date: 20120301

ACTIVE INGREDIENTS: Oxybenzone 0.56 mL/14 mL; Avobenzone 0.28 mL/14 mL; Octisalate 0.7 mL/14 mL; Homosalate 1.4 mL/14 mL; OCTOCRYLENE 0.28 mL/14 mL
INACTIVE INGREDIENTS: Water; Butylene Glycol; C12-15 Alkyl Benzoate

Timewise Day Solution sunscreen SPF 35 14ml

ACTIVE INGREDIENT

Active Ingredients ; HOMOSALATE (10% w/w) ,OCTISALATE(5% w/w),OXYBENZONE(4%w/w), OCOCRYLENE (2% w/w), AVOBENZONE(2% w/w)

WARNINGS

Warnings; For external use only. Not to be swalloed. Avoid contact with the eyes. Discontinue use if signs of irritation or rash appear.

Keep out of reach of children. Do not stay too long in the sun, even while using a sunscreen product.

INDICATIONS AND USAGE

Indication; Broad-spectrum UVA/UVB protection.

INACTIVE INGREDIENT

Water,Dimethicone, Butylene Glycol,Styrene/Acrylates Copolymer,C12-15 Alkyl Benzoate,Dicapryl Carbonate,Glycerin,Ceteareth-25,Dimethicone Crosspolymer,Magnesium Aluminum Silicate, Acetyl Dipeptide-1,Cetyl Ester, Plankton Extract,Hydrolyzed Algin, Adenosin, Pentylene Glycol , Tocopheryl Acetate,Crithmum Marithimum Extract,Ascorbic Acid,Hydrogenated Lecithin,Hydroxyethylcellulose,Dipropylene Glycol,Dibenzoate Acrylate / C12-22 Alkyl Methacrylate Crosspolymer ,Disodium Ethylene Dicocamide PEG-15 Disulfate,Sorbic Acid ,Caprylyl Glycol, PPG-15 Stearyl Ether Benzoate,Propylene Glycol , Xanthan Gum, Cyclopentasiloxane, PEG-75,PEG-150,PEG-6 Cetyl Dimethicone,PEG-4 Laurate,Laureth-3 ,Disodium EDTA , Ammonium Hydroxide,Iodopropyl Butylcarbamate,Methylparaben,Phenoxyethanol